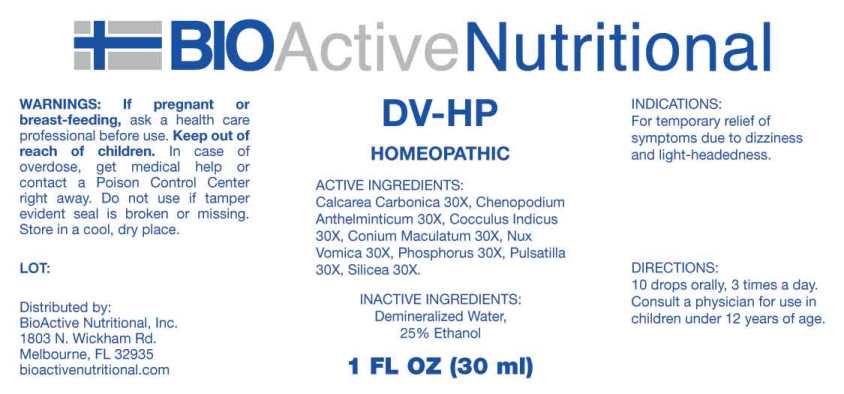 DRUG LABEL: DV HP
NDC: 43857-0610 | Form: LIQUID
Manufacturer: BioActive Nutritional, Inc.
Category: homeopathic | Type: HUMAN OTC DRUG LABEL
Date: 20240105

ACTIVE INGREDIENTS: OYSTER SHELL CALCIUM CARBONATE, CRUDE 30 [hp_X]/1 mL; DYSPHANIA AMBROSIOIDES WHOLE 30 [hp_X]/1 mL; ANAMIRTA COCCULUS SEED 30 [hp_X]/1 mL; CONIUM MACULATUM FLOWERING TOP 30 [hp_X]/1 mL; STRYCHNOS NUX-VOMICA SEED 30 [hp_X]/1 mL; PHOSPHORUS 30 [hp_X]/1 mL; PULSATILLA VULGARIS WHOLE 30 [hp_X]/1 mL; SILICON DIOXIDE 30 [hp_X]/1 mL
INACTIVE INGREDIENTS: WATER; ALCOHOL

DRUG FACTS:

ACTIVE INGREDIENTS:

CALCAREA CARBONICA 30X, CHENOPODIUM ANTHELMINTICUM 30X, COCCULUS INDICUS 30X, CONIUM MACULATUM 30X, NUX VOMICA 30X, PHOSPHORUS 30X, PULSATILLA (VULGARIS) 30X, SILICEA 30X.

INDICATIONS:

For temporary relief of symptoms due to dizziness and light-headedness.

WARNINGS:

If pregnant or breast-feeding, ask a health care professional before use.

Keep out of reach of children. In case of overdose, get medical help or contact a Poison Control Center right away.

Do not use if tamper evident seal is broken or missing.

Store in cool, dry place.

KEEP OUT OF REACH OF CHILDREN:

In case of overdose, get medical help or contact a Poison Control Center right away.

DIRECTIONS:

10 drops orally, 3 times a day. Consult a physician for use in children under 12 years of age.

INDICATIONS:

For temporary relief of symptoms due to dizziness and light-headedness.

INACTIVE INGREDIENTS:

Demineralized Water, 25% Ethanol

QUESTIONS:

Distributed by:

BioActive Nutritional, Inc.

1803 N. Wickham Rd.

Melbourne, FL 32935

bioactivenutritional.com

PACKAGE LABEL DISPLAY:

BioActive Nutritional

DV-HP

HOMEOPATHIC

1 FL OZ (30 ml)